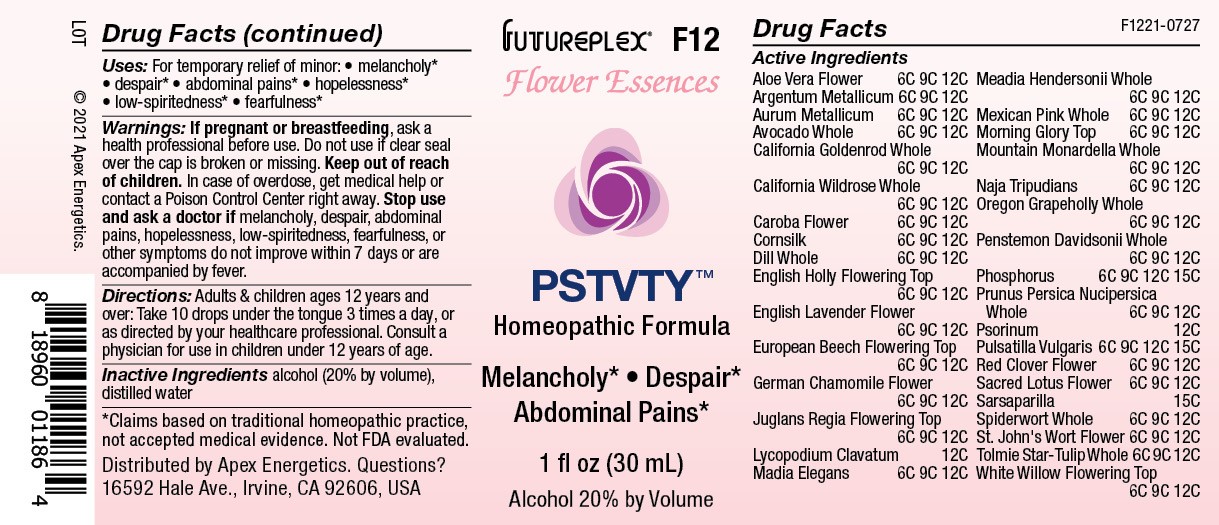 DRUG LABEL: F12
NDC: 63479-0612 | Form: SOLUTION/ DROPS
Manufacturer: Apex Energetics Inc.
Category: homeopathic | Type: HUMAN OTC DRUG LABEL
Date: 20240108

ACTIVE INGREDIENTS: NAJA NAJA VENOM 12 [hp_C]/1 mL; PHOSPHORUS 15 [hp_C]/1 mL; PRUNUS PERSICA VAR. NUCIPERSICA WHOLE 12 [hp_C]/1 mL; PULSATILLA VULGARIS WHOLE 15 [hp_C]/1 mL; TRIFOLIUM PRATENSE FLOWER 12 [hp_C]/1 mL; NELUMBO NUCIFERA FLOWER 12 [hp_C]/1 mL; PERSEA AMERICANA WHOLE 12 [hp_C]/1 mL; ALOE VERA FLOWER 12 [hp_C]/1 mL; FAGUS SYLVATICA FLOWERING TOP 12 [hp_C]/1 mL; JUGLANS REGIA FLOWERING TOP 12 [hp_C]/1 mL; CORN SILK 12 [hp_C]/1 mL; LAVANDULA ANGUSTIFOLIA SUBSP. ANGUSTIFOLIA FLOWER 12 [hp_C]/1 mL; SARSAPARILLA 15 [hp_C]/1 mL; TRADESCANTIA OCCIDENTALIS WHOLE 12 [hp_C]/1 mL; ROSA CALIFORNICA WHOLE 12 [hp_C]/1 mL; SILVER 12 [hp_C]/1 mL; GOLD 12 [hp_C]/1 mL; ANETHUM GRAVEOLENS WHOLE 12 [hp_C]/1 mL; ILEX AQUIFOLIUM FLOWERING TOP 12 [hp_C]/1 mL; CALOCHORTUS TOLMIEI WHOLE 12 [hp_C]/1 mL; JACARANDA CAROBA FLOWER 12 [hp_C]/1 mL; LYCOPODIUM CLAVATUM SPORE 12 [hp_C]/1 mL; MADIA ELEGANS WHOLE 12 [hp_C]/1 mL; IPOMOEA PURPUREA TOP 12 [hp_C]/1 mL; CHAMOMILE 12 [hp_C]/1 mL; SOLIDAGO CALIFORNICA WHOLE 12 [hp_C]/1 mL; SILENE LACINIATA WHOLE 12 [hp_C]/1 mL; HYPERICUM PERFORATUM FLOWER 12 [hp_C]/1 mL; PRIMULA HENDERSONII WHOLE 12 [hp_C]/1 mL; MONARDELLA ODORATISSIMA WHOLE 12 [hp_C]/1 mL; BERBERIS AQUIFOLIUM WHOLE 12 [hp_C]/1 mL; PENSTEMON DAVIDSONII WHOLE 12 [hp_C]/1 mL; SCABIES LESION LYSATE (HUMAN) 12 [hp_C]/1 mL; SALIX ALBA FLOWERING TOP 12 [hp_C]/1 mL
INACTIVE INGREDIENTS: ALCOHOL; WATER

F12

Active Ingredients
Aloe Vera Flower | 6C 9C 12C
Argentum Metallicum | 6C 9C 12C
Aurum Metallicum | 6C 9C 12C
Avocado Whole | 6C 9C 12C
California Goldenrod Whole | 6C 9C 12C
California Wildrose Whole | 6C 9C 12C
Caroba Flower | 6C 9C 12C
Cornsilk | 6C 9C 12C
Dill Whole | 6C 9C 12C
English Holly Flowering Top | 6C 9C 12C
English Lavender Flower | 6C 9C 12C
European Beech Flowering Top | 6C 9C 12C
German Chamomile Flower | 6C 9C 12C
Juglans Regia Flowering Top | 6C 9C 12C
Lycopodium Clavatum | 12C
Madia Elegans | 6C 9C 12C
Meadia Hendersonii Whole | 6C 9C 12C
Mexican Pink Whole | 6C 9C 12C
Morning Glory Top | 6C 9C 12C
Mountain Monardella Whole | 6C 9C 12C
Naja Tripudians | 6C 9C 12C
Oregon Grapeholly Whole | 6C 9C 12C
Penstemon Davidsonii Whole | 6C 9C 12C
Phosphorus | 6C 9C 12C 15C
Prunus Persica Nucipersica Whole | 6C 9C 12C
Psorinum | 12C
Pulsatilla Vulgaris | 6C 9C 12C 15C
Red Clover Flower | 6C 9C 12C
Sacred Lotus Flower | 6C 9C 12C
Sarsaparilla | 15C
Spiderwort Whole | 6C 9C 12C
St. John's Wort Flower | 6C 9C 12C
Tolmie Star-Tulip Whole | 6C 9C 12C
White Willow Flowering Top | 6C 9C 12C

INDICATIONS AND USAGE

Uses:

For temporary relief of minor:

melancholy*

despair*

abdominal pains*

hopelessness*

low-spiritedness*

fearfulness*

*Claims based on traditional homeopathic practice, not accepted medical evidence. Not FDA evaluated.

Warnings:

PREGNANCY OR BREAST FEEDING

If pregnant or breastfeeding, ask a health professional before use.

Do not use if clear seal over the cap is broken or missing.

Keep out of reach of children. In case of overdose, get medical help or contact a Poison Control Center right away.

Stop use and ask a doctor if melancholy, despair, abdominal pains, hopelessness, low-spiritedness, fearfulness, or other symptoms do not improve within 7 days or are accompanied by fever.

Directions:

Adults & children ages 12 years and over: Take 10 drops under the tongue 3 times a day, or as directed by your healthcare professional. Consult a physician for use in children under 12 years of age.

Inactive Ingredients

alcohol (20% by volume), distilled water

Distributed by Apex Energetics. Questions?

16592 Hale Ave., Irvine, CA 92606, USA

PACKAGE LABEL

FUTUREPLEX® F12

FLOWER ESSENCES

PSTVTY™

Homeopathic Formula

Melancholy*

Despair*

Abdominal Pains*

1 fl oz (30 mL)

Alcohol 20% by Volume